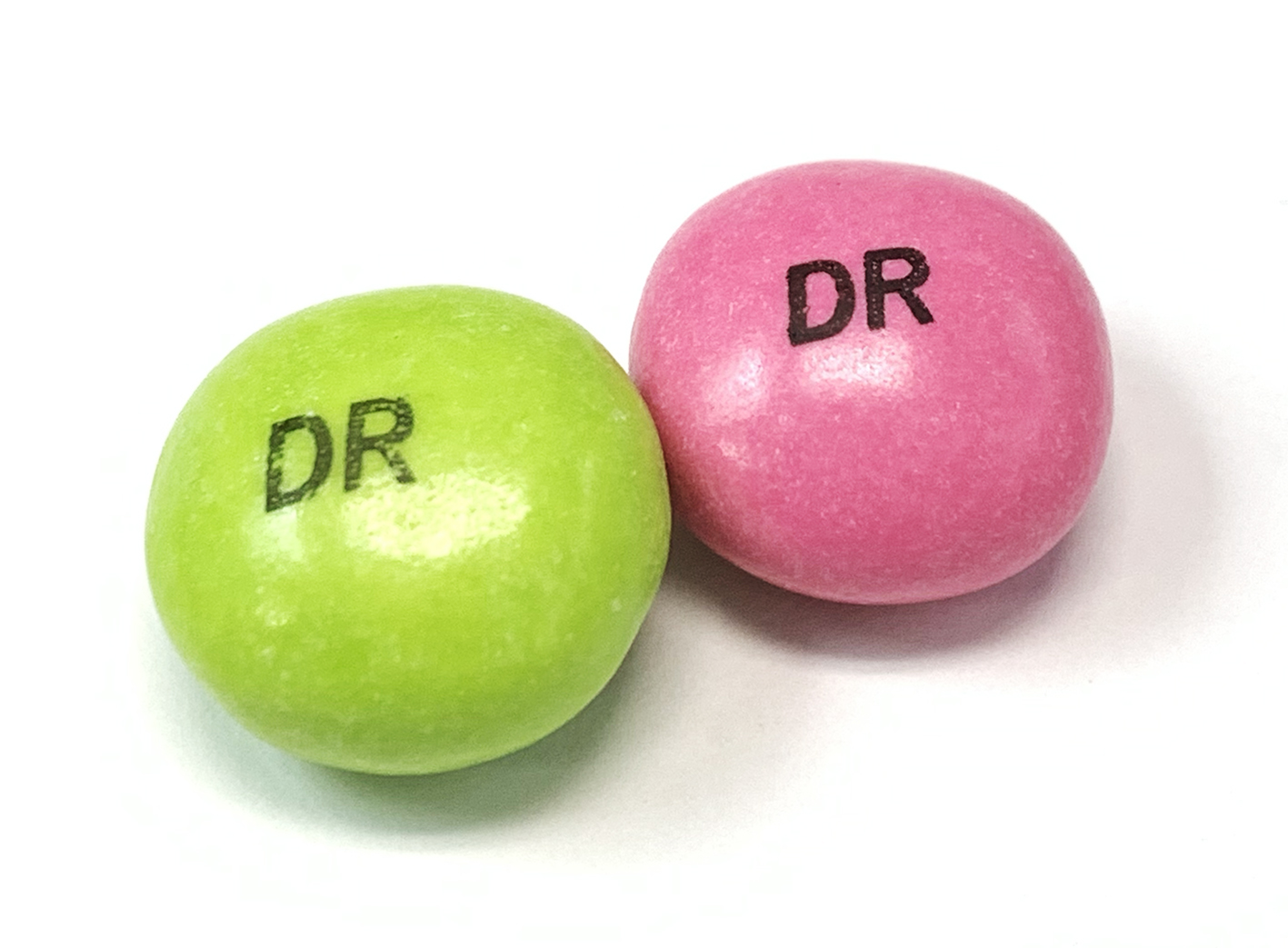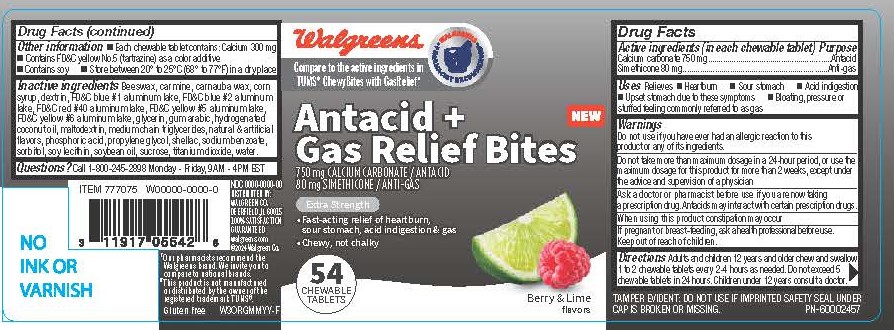 DRUG LABEL: Walgreens Cherry Berry Lime Antacid HBG 54ct
NDC: 0363-9953 | Form: TABLET, CHEWABLE
Manufacturer: Walgreens
Category: otc | Type: HUMAN OTC DRUG LABEL
Date: 20251221

ACTIVE INGREDIENTS: CALCIUM CARBONATE 750 mg/1 1; DIMETHICONE 80 mg/1 1
INACTIVE INGREDIENTS: WATER

Calcium Carbonate 750 mg
Simethicone 80 mg

Active ingredients (in each chewable tablet)

Calcium Carbonate 750 mg

Simethicone 80 mg

Purpose

Antacid

Anti-gas

INDICATIONS AND USAGE

Uses Relieves

- Heartburn
- Sour stomach
- Acid indigestion
- Upset stomach due to these symptoms
- Bloating, pressure or stuffed feeling commonly referred to as gas

Warnings

Do not use if you have ever had an allergic reaction to this product or any of its ingredients.

Do not take more than maximum dosage in a 24-hour period, or use the maximum dosage for this product for more than 2 weeks, except under the advice and supervision of a physician.

Ask a doctor or pharmacist before use if you are now taking a prescription drug. Antacids may interact with certain prescription drugs.

When using this product constipation may occur.

PREGNANCY OR BREAST FEEDING

If pregnant or breast-feeding, ask a health professional before use.

Keep out of reach of children.

Directions

Adults and children 12 years and older chew and swallow 1 to 2 chewable tablets every 2-4 hours as needed. Do not exceed 5 chewable tablets in 24 hours. Children under 12 years consult a doctor.

Other information

- Each chewabe tablet contains: Calcium 300 mg
- Contains FD&C yellow No. 5 (tartrazine) as a color additive
- Contains soy
- Store between 20° to 25°C (68° to 77°F) in a dry place

INACTIVE INGREDIENT

Inactive ingredients: Beeswax, carmine, carnauba wax, corn syrup, dextrin, FD&C blue #1 aluminum lake, FD&C blue #2 aluminum lake, FD&C red #40 aluminum lake, FD&C yellow #5 aluminum lake, FD&C yellow #6 aluminum lake, glycerin, gum arabic, hydrogenated coconut oil, maltodextrin, medium chain triglycerides, natural & artificial flavors, phosphoric acid, propylene glycol, shellac, sodium benzoate, sorbitol, soy lecithin, soybean oil, sucrose, titanium dioxide, water.

QUESTIONS

Questions? Call 1-800-245-2898 Monday - Friday, 9AM - 4PM EST